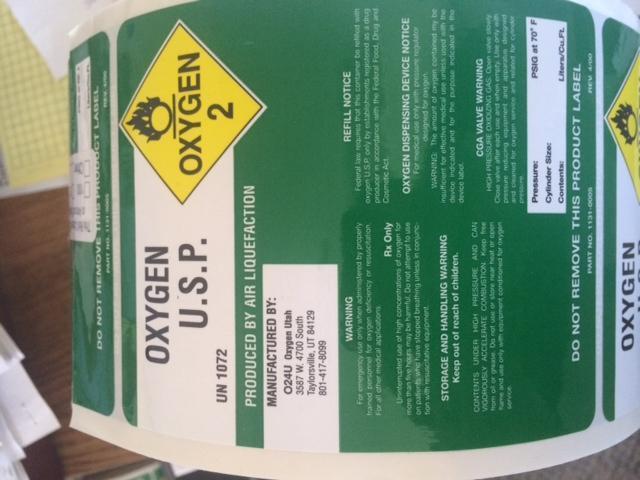 DRUG LABEL: OXYGEN
NDC: 69044-123 | Form: GAS
Manufacturer: OXYGEN UTAH
Category: prescription | Type: HUMAN PRESCRIPTION DRUG LABEL
Date: 20140612

ACTIVE INGREDIENTS: OXYGEN 210 mL/1 L

Cylinder Label

WARNING

For Emergency use only when administered by properly trained personnel for oxygen deficiency or resuscitation. For all other medical applicatios.

RX ONLY

Uninterrupted use of high concentrations of oxygen for more than five hours may be harmful. Do not attempt to use on patients who have stopped breathing unless in conjunction with resuscitative equipment.

PRESSURE:_________PSIGat 70 F

Cylinder Size:_________

Contents:__________ Liters/Cu.Ft.

STORAGE AND HANDLING WARNING
Keep out of reach of children.

CONTENTS UNDER HIGH PRESSURE AND CAN VIGOROUSLY ACCELERATE COMBUSTION. Keep free from oil or grease. Do not use or store near heat or open flame and use only with equipment condition for oxygen service.

REFILL NOTICE

Federal law requires that this container be refilled with oxygen U.S.P. only by estalishements registered as a drug producer in accordance with the Federal Food, Drug and Cosmetic Act.

OXYGEN DISPENSING DEVICE NOTICE

For medical use only with pressure regulator designed for oxygen.

WARNING: The amount of oxygen contained may be insufficient for medical use unless used with the device indicaed and for the purpose indicated in the device label.

CGA VALUE WARNING

HIGH PRESSURE OXIDIZING GAS: Open valve slowly. Close valve after each use and when empty. Use only with Pressure reducing equipment and apparatus designed and cleaned for oxygen service and related for cylinder pressure.